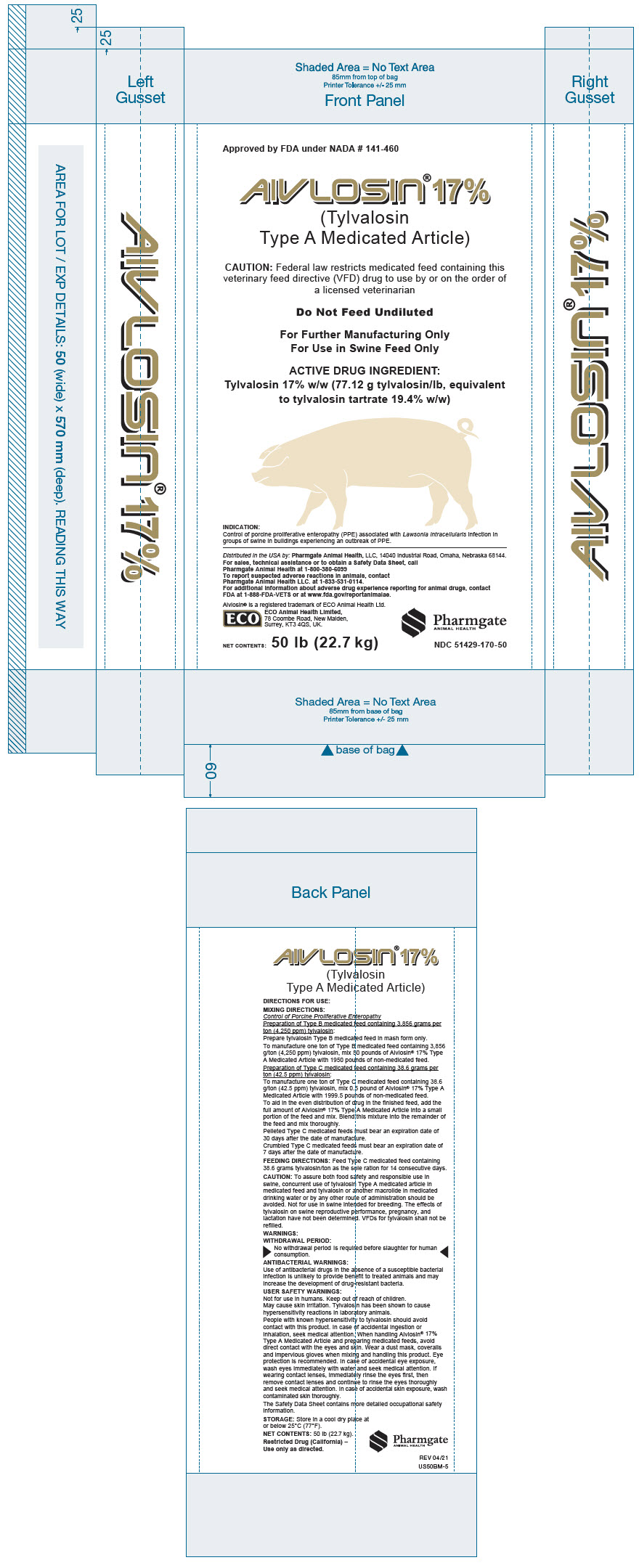 DRUG LABEL: Aivlosin
NDC: 51429-170 | Form: GRANULE
Manufacturer: Pharmgate Animal Health
Category: animal | Type: VFD TYPE A MEDICATED ARTICLE ANIMAL DRUG LABEL
Date: 20250827

ACTIVE INGREDIENTS: Tylvalosin 170 g/1 kg

Aivlosin®17%
(Tylvalosin Type A Medicated Article)

CAUTION: Federal law restricts medicated feed containing this veterinary feed directive (VFD) drug to use by or on the order of a licensed veterinarian.

Do Not Feed Undiluted
For Further Manufacturing Only
For Use in Swine Feed Only

ACTIVE DRUG INGREDIENT: Tylvalosin 17% w/w (77.12 g tylvalosin/lb, equivalent to tylvalosin tartrate 19.4% w/w)

NADA 141-460 Approved by FDA.

VETERINARY INDICATIONS

INDICATION:

Swine: Control of porcine proliferative enteropathy (PPE) associated with Lawsonia intracellularis infection in groups of swine in buildings experiencing an outbreak of PPE.

DOSAGE AND ADMINISTRATION

DIRECTIONS FOR USE:

MIXING DIRECTIONS:

Swine:

Control of Porcine Proliferative Enteropathy

Preparation of Type B medicated feed containing 3,856 grams per ton (4,250 ppm) tylvalosin:

Prepare tylvalosin Type B medicated feed in mash form only.

To manufacture one ton of Type B medicated feed containing 3,856 g/ton (4,250 ppm) tylvalosin, mix 50 pounds of Aivlosin® 17% Type A Medicated Article with 1950 pounds of non-medicated feed.

Preparation of Type C medicated feed containing 38.6 grams per ton (42.5 ppm) tylvalosin:

To manufacture one ton of Type C medicated feed containing 38.6 g/ton (42.5 ppm) tylvalosin, mix 0.5 pound of Aivlosin® 17% Type A Medicated Article with 1999.5 pounds of non-medicated feed.

To aid in the even distribution of drug in the finished feed, add the full amount of Aivlosin® 17% Type A Medicated Article into a small portion of the feed and mix. Blend this mixture into the remainder of the feed and mix thoroughly. Pelleted Type C medicated feeds must bear an expiration date of 30 days after the date of manufacture.

Crumbled Type C medicated feeds must bear an expiration date of 7 days after the date of manufacture.

FEEDING DIRECTIONS: Feed Type C medicated feed containing 38.6 grams tylvalosin/ton as the sole ration for 14 consecutive days.

CAUTION: To assure both food safety and responsible use in swine, concurrent use of tylvalosin Type A medicated article in medicated feed and tylvalosin or another macrolide in medicated drinking water or by any other route of administration should be avoided. Not for use in swine intended for breeding. The effects of tylvalosin on swine reproductive performance, pregnancy, and lactation have not been determined. VFDs for tylvalosin shall not be refilled.

WARNINGS:

WITHDRAWAL PERIOD:

No withdrawal period is required before slaughter for human consumption.

ANTIBACTERIAL WARNINGS:

Use of antibacterial drugs in the absence of a susceptible bacterial infection is unlikely to provide benefit to treated animals and may increase the development of drug-resistant bacteria.

SAFE HANDLING WARNING

USER SAFETY WARNINGS:

Not for use in humans. Keep out of reach of children.

May cause skin irritation. Tylvalosin has been shown to cause hypersensitivity reactions in laboratory animals. People with known hypersensitivity to tylvalosin should avoid contact with this product. In case of accidental ingestion or inhalation, seek medical attention. When handling Aivlosin® 17% Type A Medicated Article and preparing medicated feeds, avoid direct contact with the eyes and skin. Wear a dust mask, coveralls and impervious gloves when mixing and handling this product. Eye protection is recommended. In case of accidental eye exposure, wash eyes immediately with water and seek medical attention. If wearing contact lenses, immediately rinse the eyes first, then remove contact lenses and continue to rinse the eyes thoroughly and seek medical attention. In case of accidental skin exposure, wash contaminated skin thoroughly.

The Safety Data Sheet contains more detailed occupational safety information.

STORAGE AND HANDLING

STORAGE: Store in a cool dry place at or below 25°C (77°F).

Restricted Drug (California) - Use only as directed.

Distributed in the USA by: Pharmgate Animal Health, LLC 14040 Industrial Road, Omaha, Nebraska 68144

For sales, technical assistance or to obtain a Safety Data Sheet, call Pharmgate Animal Health at 1-800-380-6099

To report suspected adverse drug events, contact Pharmgate Animal Health LLC at 1-833-531-0114. For additional information about adverse drug experience reporting for animal drugs, contact FDA at 1-888-FDA-VETS or at www.fda.gov/reportanimalae.

Pharmgate Animal Health has contracted with the ASPCA Animal Product Safety Service to collect human and animal suspected adverse drug events reports for this product.

Aivlosin® is a registered trademark of ECO Animal Health Ltd.

ECO Animal Health Limited, 78 Coombe Road, New Malden, Surrey, KT3 4QS, UK.

NDC 51429-170-50

Net Contents:
50 LB (22.7 Kg)

PRINCIPAL DISPLAY PANEL - 22.7 kg Bag

NADA 141-460
Approved by FDA.

AIVLOSIN®17%
(Tylvalosin
Type A Medicated Article)

CAUTION: Federal law restricts medicated feed containing this
veterinary feed directive (VFD) drug to use by or on the order of
a licensed veterinarian

Do Not Feed Undiluted

For Further Manufacturing Only
For Use in Swine Feed Only

ACTIVE DRUG INGREDIENT:
Tylvalosin 17% w/w (77.12 g tylvalosin/lb, equivalent
to tylvalosin tartrate 19.4% w/w)

INDICATION:
Swine: Control of porcine proliferative enteropathy (PPE) associated with Lawsonia intracellularis
infection in groups of swine in buildings experiencing an outbreak of PPE.

Distributed in the USA by: Pharmgate Animal Health, LLC, 14040 Industrial Road, Omaha, Nebraska 68144.

For sales, technical assistance or to obtain a Safety Data Sheet, call
Pharmgate Animal Health at 1-800-380-6099

To report suspected adverse drug events, contact the ASPCA Animal Product Safety Service at
1-800-345-4735 or the FDA at 1-888-FDA-VETS

Pharmgate Animal Health has contracted with the ASPCA Animal Product Safety Service to collect human
and animal suspected adverse drug events reports for this product.

Aivlosin® is a registered trademark of ECO Animal Health Ltd.

ECO Animal Health Limited,
78 Coombe Road, New Malden,
Surrey, KT3 4QS, UK.

NET CONTENTS:
50 lb (22.7 kg)

Pharmgate
ANIMAL HEALTH

NDC 51429-170-50